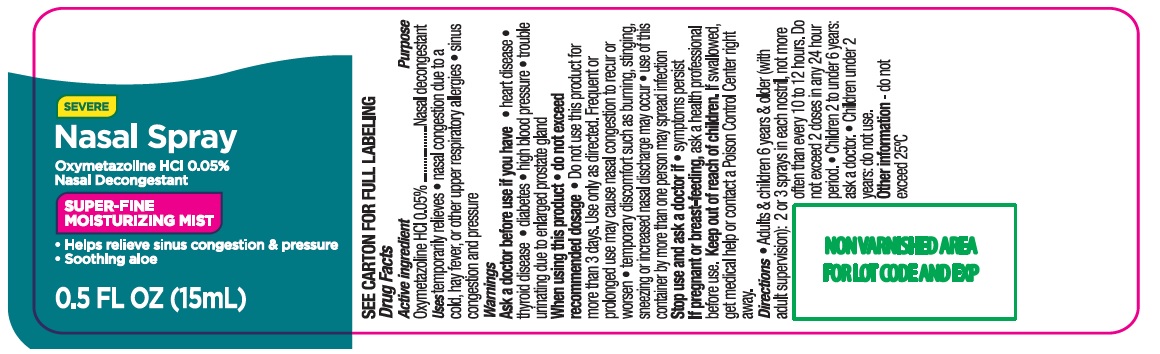 DRUG LABEL: Severe Nasal
NDC: 73492-715 | Form: SPRAY
Manufacturer: ALAINA HEALTHCARE PRIVATE LIMITED
Category: otc | Type: HUMAN OTC DRUG LABEL
Date: 20251209

ACTIVE INGREDIENTS: OXYMETAZOLINE HYDROCHLORIDE 0.05 g/100 mL
INACTIVE INGREDIENTS: ALOE VERA LEAF; BENZALKONIUM CHLORIDE; EDETATE DISODIUM ANHYDROUS; POLYETHYLENE GLYCOL, UNSPECIFIED; POVIDONE, UNSPECIFIED; PROPYLENE GLYCOL; WATER; SODIUM PHOSPHATE, DIBASIC, UNSPECIFIED FORM; SODIUM PHOSPHATE, MONOBASIC, ANHYDROUS

Severe Nasal Spray

Drug Facts

Active ingredient Purpose

Oxymetazoline hydrochloride 0.05% ............................................................................................... Nasal decongestant

Uses

temporarily relieves

- nasal congestion due to a cold, hay fever, or other upper respiratory allergies
- sinus congestion and pressure

WARNINGS

Warnings

Ask a doctor before use if you have

- heart disease
- thyroid disease
- diabetes
- high blood pressure
- trouble urinating due to an enlarged prostate gland

When using this product

- do not exceed recommended dosage
- Do not use this product for more than 3 days. Use only as directed. Frequent or prolonged use may cause nasal congestion to recur or worsen.
- temporary discomfort such as burning, stinging, sneezing or increased nasal discharge may occur
- use of this container by more than one person may spread infection

Stop use and ask a doctor if

- symptoms persist

PREGNANCY OR BREAST FEEDING

If pregnant or breast-feeding,ask a health professional before use.

Keep out of reach of children.

If swallowed, get medical help or contact a Poison Control Center right away.

Directions

- Adults & children 6 years & older (with adult supervision): 2 or 3 sprays in each nostril, not more often than every 10 to 12 hours. Do not exceed 2 doses in any 24 hour period.
- Children 2 to under 6 years: ask a doctor.
- Children under 2 years: do not use.

Other information -do not exceed 25°C

Inactive ingredients

aloe barbadensis leaf extract, benzalkonium chloride, disodium EDTA, polyethylene glycol, PVP, propylene glycol, purified water, sodium phosphate dibasic, sodium phosphste monobasic

Principal Display Panel

SEVERE Nasal Spray
Oxymetazoline HCl 0.05 %
Nasal Decongestant
SUPER-FINE Moisturizing MIST
- Helps relieve sinus congestion & pressure
- Soothing aloe
0.5 FL OZ (15mL)